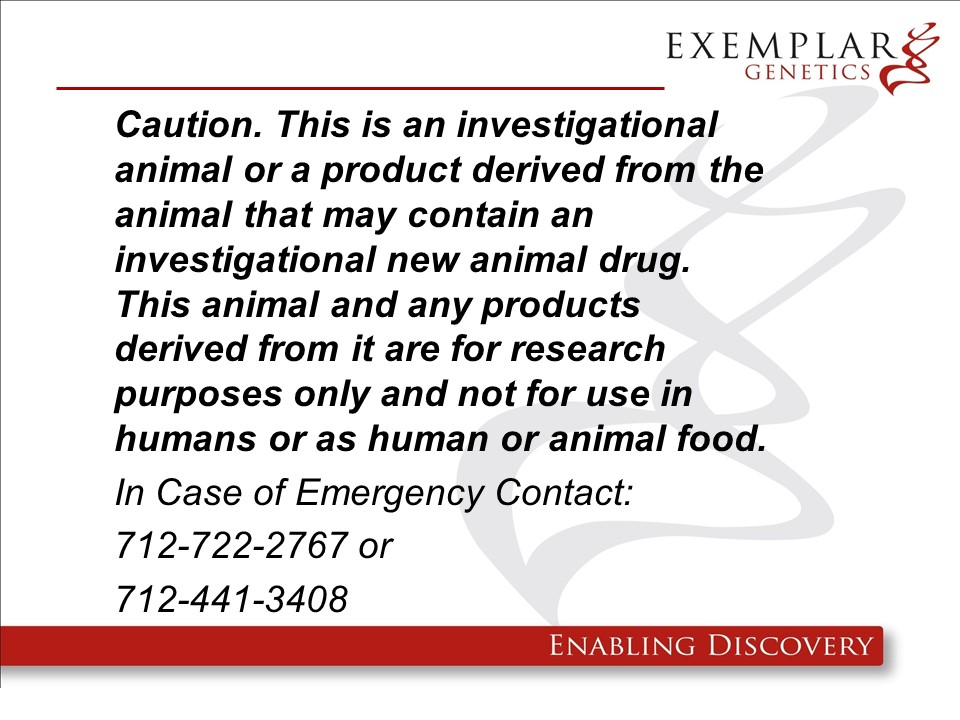 DRUG LABEL: ExeGen NF1 miniswine
NDC: 86093-1903 | Form: NOT APPLICABLE
Manufacturer: Exemplar Genetics, Llc
Category: other | Type: INTENTIONAL ANIMAL GENOMIC ALTERATION LABEL
Date: 20250616

ACTIVE INGREDIENTS: NF1 RDNA CONSTRUCT AT EXON 42 IN YUCATAN MINIPIG (+/-) 1 [arb'U]/1 [arb'U]

pNF1-Blast Excised in miniswine

ExeGen NF1 miniswine are geneticaly engineered yucatan miniature swine containing the rDNA construct pNF1-Blast which exibit similar phenotypes to human patients with Neurofibromatosis. These pigs are intended to be used as large animal models of the human disease. We will not be requesting a food use authorizaiton and the carcasses and all materials generated from these animals will be destroyed by incineration.

Product Definition: A specific line of Yucatan miniature pigs (Sus scrofa domesticus), including heterozygous offspring resulting from a heterozygous founder, in which the NF1 gene has been disrupted by the homologous recombination of a single copy of a mutated NF1-PGK construct resulting in the deletion of exon 42 for use in biomedical research. The final sellable animal will be a heterozygous NF1 +/Ex42del Blast excised miniswine.

Warning: This product is from a genetically engineered animal and may contain an investigational new animal drug. It is for research purposes only and not for use in humans or as food/feed unless authorization has been granted by the US Food and Drug Administration. In case of emergency or release contact Exemplar Genetics at 712-722-2767 or 712-441-3408.